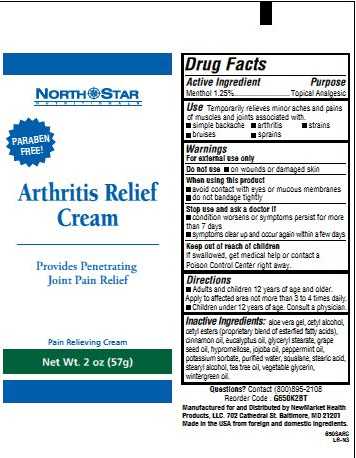 DRUG LABEL: Arthritis Relief 
NDC: 50972-272 | Form: CREAM
Manufacturer: NewMarket Health Products LLC
Category: otc | Type: HUMAN OTC DRUG LABEL
Date: 20120413

ACTIVE INGREDIENTS: Menthol 12.5 mg/1 g
INACTIVE INGREDIENTS: Aloe Vera Leaf; Cetyl Alcohol; Cetyl Esters Wax; Cinnamon Oil; Eucalyptus Oil; Glyceryl Monostearate; Grape Seed Oil; Hypromelloses; Jojoba Oil; Peppermint Oil; Potassium Sorbate; Water; Squalane; Stearic Acid; Stearyl Alcohol; Tea Tree Oil; Glycerin; Methyl Salicylate

Drug Facts

Active Ingredient
Menthol 1.25%

Purpose

Topical Analgesic

INDICATIONS AND USAGE

UseTemporarily relieves minor aches and pains of muscles and joints associated with:

- simple backache
- arthritis
- strains
- bruises
- sprains

Warnings

For external use only

Do not use

- on wounds or damaged skin

WHEN USING

Enter section text here

Stop use and ask a doctor if

- condition worsens or symptoms persist for more than 7 days
- symptoms clear up and occur again within a few days

Keep out of reach of children.
If swallowed, get medical help or contact a Poison Control Center right away.

Directions

- Adult and children 12 years of age or older: Apply to affected area not more than 3 to 4 times daily.
- Children under 12 years of age: Consult a physician.

INACTIVE INGREDIENT

Inactive Ingredients: aloe vera gel, cetyl alcohol, cetyl esters (proprietary blend of esterfied fatty acids), cinnamon oil, eucalyptus oil, glyceryl stearate, grape seed oil, hypromellose, jojoba oil, peppermint oil, potassium sorbate, purified water, squalane, stearic acid, stearyl alcohol, tea tree oil, vegetable glycerin, wintergreen oil

Questions? Contact (800) 895-2108.

Reorder Code: G650K2BT

Manufactured for and Distributed by NewMarket Health

Products, LLC. 702 Cathedral St. Baltimore, MD 21201

Made in the USA from foreign and domestic ingredients.

PACKAGE LABEL

North Star

Nutritionals

Paraben Free!

Arthritis Relief

Cream

Provides Penetrating

Joint Pain Relief

Pain Relieving Cream

Net Wt. 2 oz (57g)